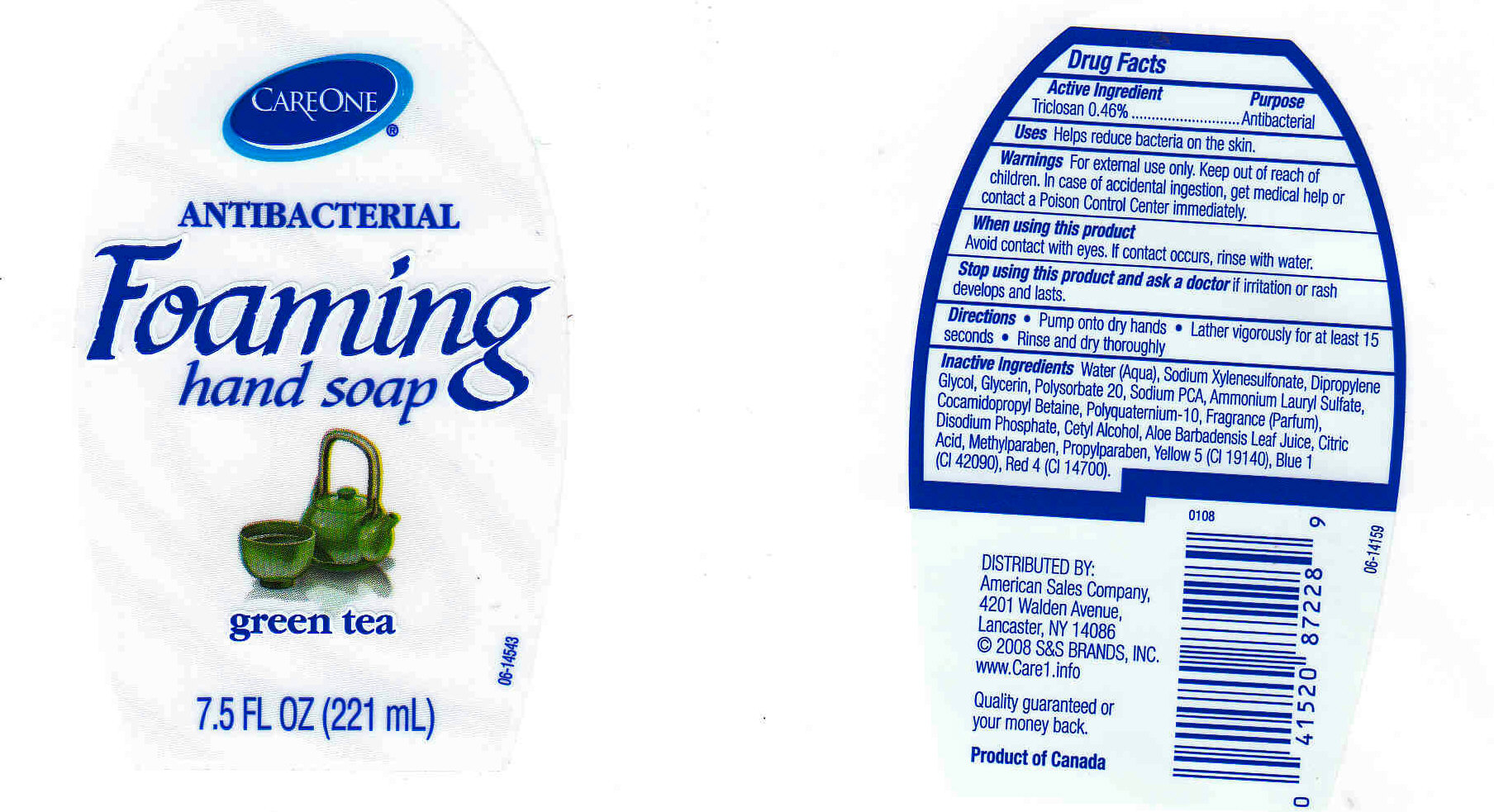 DRUG LABEL: CARE ONE Antibacterial Foaming Hand Soap 
NDC: 63148-165 | Form: LIQUID
Manufacturer: Apollo Health and Beauty Care
Category: otc | Type: HUMAN OTC DRUG LABEL
Date: 20090717

ACTIVE INGREDIENTS: TRICLOSAN 0.4600 mL/100 mL
INACTIVE INGREDIENTS: WATER 74.8937 mL/100 mL; BENZENESULFONIC ACID 10.0000 mL/100 mL; DIPROPYLENE GLYCOL 5.0000 mL/100 mL; GLYCERIN  5.0000 mL/100 mL; POLYSORBATE 20 1.0000 mL/100 mL; SODIUM PYRROLIDONE CARBOXYLATE 1.0000 mL/100 mL; AMMONIUM LAURYL SULFATE  1.0000 mL/100 mL; COCAMIDOPROPYL BETAINE 1.0000 mL/100 mL; CETRIMONIUM CHLORIDE 0.0500 mL/100 mL; SODIUM PHOSPHATE, DIBASIC, DIHYDRATE 0.2000 mL/100 mL; CETYL ALCOHOL  0.0500 mL/100 mL; ALOE VERA LEAF 0.0010 mL/100 mL; CITRIC ACID  0.04500 mL/100 mL; METHYLPARABEN 0.2000 mL/100 mL; PROPYLPARABEN  0.1000 mL/100 mL; FD&C YELLOW NO. 5 0.0001 mL/100 mL; FD&C BLUE NO. 1 0.0001 mL/100 mL; FD&C RED NO. 4 0.0001 mL/100 mL

CARE ONE FOAMING ANTIBACTERIAL HAND SOAP - GREEN TEA

ACTIVE INGREDIENT

TRICLOSAN 0.46% (PURPOSE: ANTIBACTERIAL)

USES

HELPS TO REDUCE BACTERIA ON THE SKIN.

WARNINGS

FOR EXTERNAL USE ONLY. KEEP OUT OF REACH OF CHILDREN. IN CASE OF ACCIDENTAL INGESTION, GET MEDICAL HELP OR CONTACT A POISON CONTROL CENTER IMMEDIATLEY.

WHEN USING THIS PRODUCT

AVOID CONTACT WITH EYES. IF CONTACT OCCURS, RINSE WITH WATER.

STOP USING THIS PRODUCT AND ASK DOCTOR IF

IF IRRITATION OR RASH DEVELOPS AND LASTS.

Package Front and Back Labels

MM01: Package Labels (Labels.jpg)